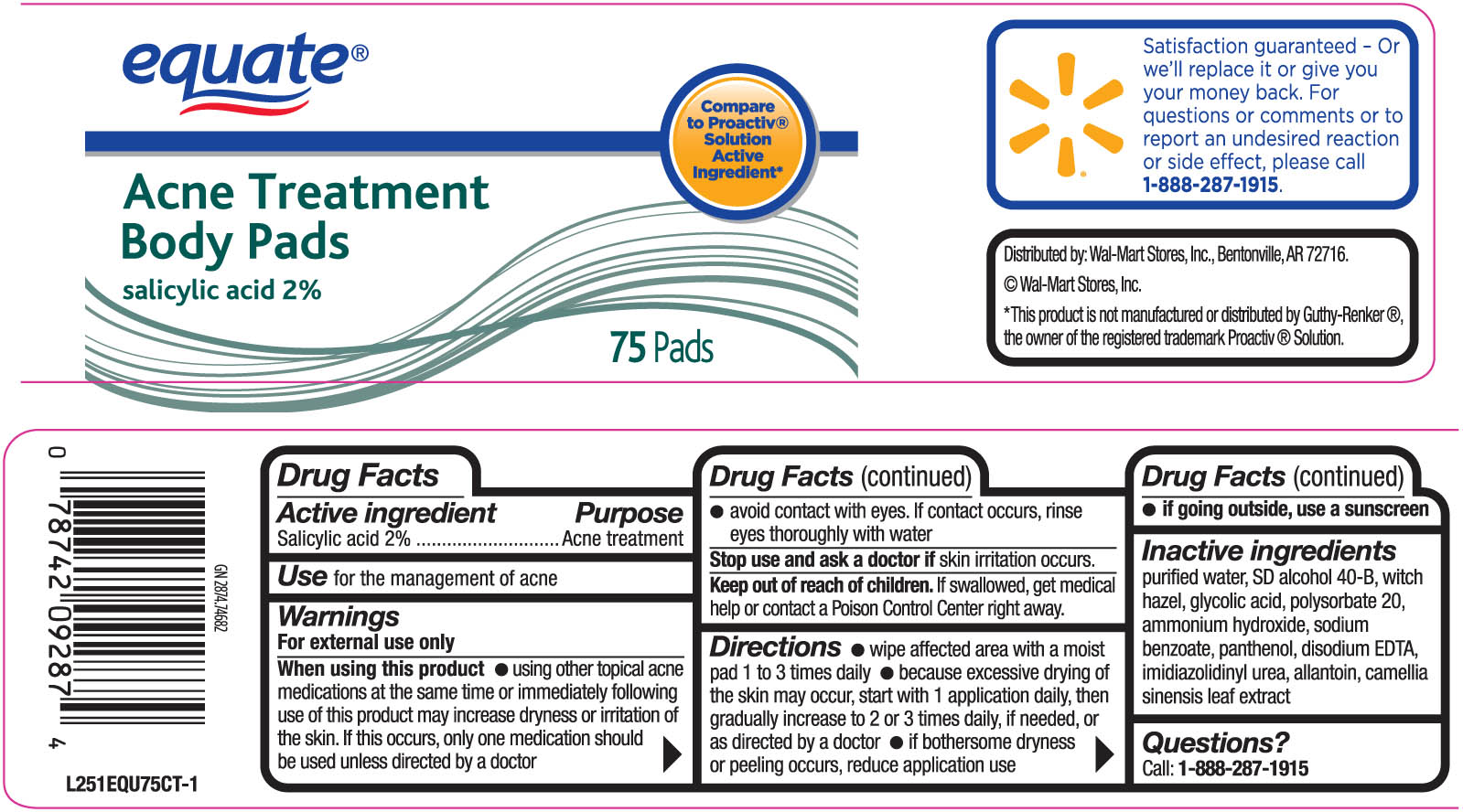 DRUG LABEL: Equate Acne Treatment Body Pads
NDC: 49035-024 | Form: SWAB
Manufacturer: Wal-Mart Stores Inc
Category: otc | Type: HUMAN OTC DRUG LABEL
Date: 20100713

ACTIVE INGREDIENTS: SALICYLIC ACID 20 mg/1 1
INACTIVE INGREDIENTS: WATER; ALCOHOL; ALLANTOIN; GREEN TEA LEAF; EDETATE DISODIUM; GLYCOLIC ACID; WITCH HAZEL; PANTHENOL; POLYSORBATE 20; SODIUM BENZOATE; DIAZOLIDINYL UREA; AMMONIA

drug facts

Active ingredient Purpose
Salicylic Acid, 2%.......................................Acne Treatment

PURPOSE

Use - for the treatment of acne

Keep out of reach of children. If swallowed, get medical help or contact a Poison
Control Center right away.

Directions

- wipe affected area with a moist pad 1 to 3 times daily
- because excessive drying of the skin may occur, start with one application daily, then gradually increase to 2 or 3 times daily, if needed or as directed by a doctor.
- if bothersome drying or peeling occurs, reduce application use.
If going outside, use a sunscreen
Questions?
Call 1-888-287-1915

Warnings
For external use only.
When using this product
- using other topical acne medications at the same time or immediately following use of this product may
increase dryness or irritation of the skin. If this occurs, only one medication should be used unless directed by a doctor.
- avoid contact with the eyes. If contact occurs, rinse eyes thoroughly with water.
Stop use and ask a doctor if skin irritation occurs.
Keep out of reach of children. If swallowed, get medical help or contact a Poison
Control Center right away.

Directions

- wipe affected area with a moist pad 1 to 3 times daily
- because excessive drying of the skin may occur, start with one application daily, then gradually increase to 2 or 3 times daily, if needed or as directed by a doctor.
- if bothersome drying or peeling occurs, reduce application use.
If going outside, use a sunscreen
Questions?
Call 1-888-287-1915

Inactive Ingredients
purified water SD alcohol 40-B, Witch Hazel, glycolic acid, polysorbate 20,
ammonium hydroxide, sodium benzoate, panthenol, disodium EDTA, imidazolidinyl urea,
allantoin, camellia sinensis leaf extract